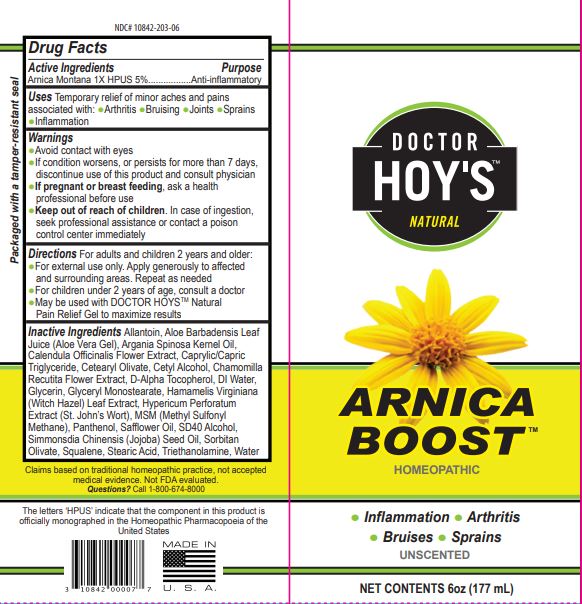 DRUG LABEL: DOCTOR HOYS Natural Arnica Boost
NDC: 10842-203 | Form: CREAM
Manufacturer: DOCTOR HOY'S, LLC
Category: homeopathic | Type: HUMAN OTC DRUG LABEL
Date: 20221205

ACTIVE INGREDIENTS: ARNICA MONTANA 5 [hp_X]/1 mL
INACTIVE INGREDIENTS: CALENDULA OFFICINALIS FLOWER; CHAMOMILE; HYPERICUM PERFORATUM; .ALPHA.-TOCOPHEROL, D-; PANTHENOL; SAFFLOWER OIL; CETEARYL OLIVATE; DIMETHYL SULFONE; ALOE VERA LEAF; WATER; WITCH HAZEL; CETYL ALCOHOL; JOJOBA OIL; ARGAN OIL

HPUS Arnica Boost

WARNINGS

Warnings: for external use only, avoid contact with eyes, Keep out of reach of children. if swallowed, get medical help or contact a Poison Control Center immediately, if condition worsens, or if symptoms persist for more than 7 days or clear up and occur again within a few days, discontinue use of this product and consult a physician, Pregnancy-breast feeding warning: if pregnant or breast feeding, ask a health professional before use, do not bandage tightly

Active Ingredients Purpose

10% Arnica Montana 1X HPUS

INDICATIONS AND USAGE

Directions: Use by itself or with DOCTOR HOY'S Natural Pain Relief Gel. For adults and children 2 years and older. "Children under 2 years of age: consult a doctor." For best results, apply generously to affected and surrounding areas. Repeat as needed.

Uses: for the temporary relief of minor aches and pains of muscles and joints due to: , inflammation, arthritis, sprains, strains, bruises

INACTIVE INGREDIENT

Inactive Ingredients: deionized water, hamamelis virginiana (witch hazel extract), isopropyl alcohol, cetyl alcohol, glycerin, tocopheryl acetate (vitamin E), aloe vera, argan oil, calendula oil, chamomile, hyperium Perforatum Extract, safflower oil, tilia cordata flower extract

PURPOSE

Uses: for the temporary relief of minor aches and pains of muscles and joints associated with: Inflammation, arthritis, sprains, strains, bruises, Expedites healing, Reduces swelling, Extends relief time, Absorbs quickly, Odorless

KEEP OUT OF REACH OF CHILDREN

Warnings: for external use only, avoid contact with eyes, Keep out of reach of children. if swallowed, get medical help or contact a Poison Control Center immediately, if condition worsens, or if symptoms persist for more than 7 days or clear up and occur again within a few days, discontinue use of this product and consult a physician, Pregnancy-breast feeding warning: if pregnant or breast feeding, ask a health professional before use, do not bandage tightly

DOSAGE AND ADMINISTRATION

Directions: Use by itself or with DOCTOR HOY'S Natural Pain Relief Gel. for adults and children 2 years and older. "Children under 2 years of age: consult a doctor." For best results, apply generously to affected and surrounding areas. Repeat as needed.

PACKAGE LABEL

An image/graphic of the product is included